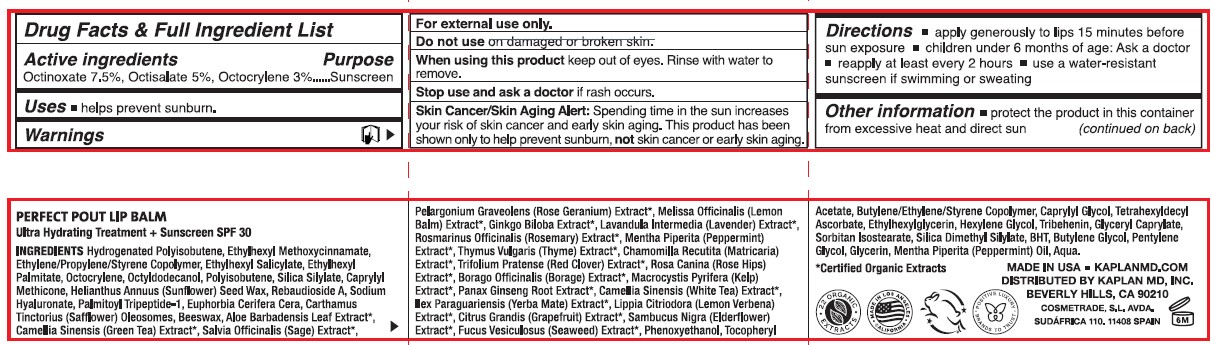 DRUG LABEL: Kaplan MD Perfect Pout Lip Balm
NDC: 84300-001 | Form: LIPSTICK
Manufacturer: KAPLAN MD INC
Category: otc | Type: HUMAN OTC DRUG LABEL
Date: 20240508

ACTIVE INGREDIENTS: OCTOCRYLENE 3 g/100 g; OCTINOXATE 7.5 g/100 g; OCTISALATE 5 g/100 g
INACTIVE INGREDIENTS: RED CLOVER; HELIANTHUS ANNUUS SEED WAX; HYDROGENATED POLYISOBUTENE (1300 MW); PENTYLENE GLYCOL; WATER; MACROCYSTIS PYRIFERA; FUCUS VESICULOSUS; BUTYLENE GLYCOL; GREEN TEA LEAF; GLYCERIN; HYALURONATE SODIUM; ALOE VERA LEAF; .ALPHA.-TOCOPHEROL ACETATE, DL-; SILICA DIMETHYL SILYLATE; REBAUDIOSIDE A; ROSEMARY; SAGE; LEMON BALM OIL; MATRICARIA CHAMOMILLA; BORAGE; PHENOXYETHANOL; WHITE TEA; TETRAHEXYLDECYL ASCORBATE; CARTHAMUS TINCTORIUS (SAFFLOWER) OLEOSOMES; GRAPEFRUIT; THYME; PANAX GINSENG ROOT OIL; TRIBEHENIN; SORBITAN ISOSTEARATE; BUTYLATED HYDROXYTOLUENE; PEPPERMINT; ETHYLHEXYLGLYCERIN; HEXYLENE GLYCOL; CAPRYLYL GLYCOL; GLYCERYL CAPRATE

Kaplan MD Perfect Pout Lip Balm (Clear)

Active Ingredients

Octinoxate 7.5%

Octisalate 5%

Octocrylene 3%

Purpose

Sunscreen

Warnings

For external use only.

Skin Cancer/Skin Agung Alert: Spending time in the sun increases your risk of skin cancer and early skin aging. This product has been shown to help prevent sunburn, not skin cancer or early skin aging.

Do not use on damaged and broken skin.

Stop use and ask a doctor if rash occurs.

When using this product keep out of eyes. Rinse with water to remove.

Other Information

- protect the product in this container from excessive heat and direct sun

Directions

- apply generously to lips 15 minutes before sun exposure
- children under 6 months of age: Ask a doctor
- reapply at least every 2 hours
- use a water-resistant sunscreen if swimming or sweating

Inactive Ingredients

Hydrogenated Polyisobutene, Ethylhexyl Methoxycinnamate, Ethylene/Propylene/Styrene Copolymer, Ethylhexyl Salicylate, Ethylhexyl Palmitate,Octocrylene, Octyldodecanol, Polyisobutene, Silica Silylate, Caprylyl Methicone, Helianthus Annuus (Sunflower) Seed Wax, Rebaudioside A, Sodium Hyaluronate, Palmitoyl Tripeptide-1, Euphorbia Cerifera Cera, Carthamus Tinctorius (Safflower) Oleoseomes, Beeswax, Aloe Barbadensis Leaf Extract*, Camellia Sinensis (Green Tea) Extract*, Salvia Officinalis (Sage) Extract*, Pelargonium Graveolens (Rose Geranium) Extract*, Melissa Officinalis (Lemon Balm) Extract*, Ginkgo Biloba Extract*, Lavandula lntermedia (Lavender) Extract*, Rosmarinus Officinalis (Rosemary) Extract*, Mentha Piperita (Peppermint) Extract*,Thymus Vulgaris (Thyme) Extract*, Chamomilla Recutita (Matricaria) Extract*,Trifolium Pratense (Red Clover) Extract*, Rosa Canina (Rose Hips) Extract*, Baraga Officinalis (Borage) Extract*, Macrocystis Pyrifera (Kelp) Extract*, Panax Ginseng Root Extract*, Camellia Sinensis (White Tea) Extract*, llex Paraguariensis (Yerba Mate) Extract*,Lippia Citriodora (Lemon Verbena) Extract*, Citrus Grandis (Grapefruit) Extract*, Sambucus Nigra (Elderflower) Extract*, Fucus Vesiculosus (Seaweed) Extract*, Phenoxyethanol, Tocopheryl Acetate, Butylene/Ethylene/Styrene Copolymer, Caprylyl Glycol, Tetrahexyldecyl Ascorbate, Ethylhexylglycerin, Hexylene Glycol, Tribehenin, Glyceryl Caprylate, Sorbitan lsostearate, Silica Dimethyl Silylate, BHT, Butylene Glycol, Pentylene Glycol, Glycerin, Mentha Piperita (Peppermint) Oil, Aqua.

Keep out of reach of children.

DOSAGE AND ADMINISTRATION

apply generously to lips 15 minutes before sun exposure